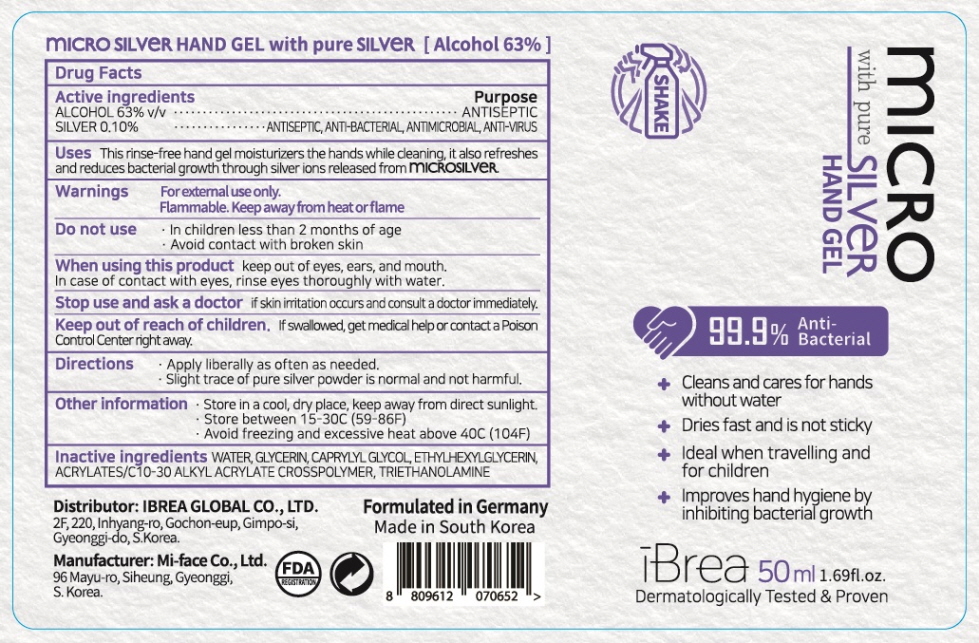 DRUG LABEL: iBrea Micro Silver Hand with Pure Silver
NDC: 78030-020 | Form: GEL
Manufacturer: IBREA GLOBAL CO.,LTD.
Category: otc | Type: HUMAN OTC DRUG LABEL
Date: 20200521

ACTIVE INGREDIENTS: ALCOHOL 31.5 mL/50 mL; SILVER 0.05 g/50 mL
INACTIVE INGREDIENTS: Water; Glycerin; CAPRYLYL GLYCOL; ETHYLHEXYLGLYCERIN; CARBOMER INTERPOLYMER TYPE A (ALLYL SUCROSE CROSSLINKED); TROLAMINE

ACTIVE INGREDIENTS

ALCOHOL 63% v/v
SILVER 0.10%

INACTIVE INGREDIENTS

WATER, GLYCERIN, CAPRYLYL GLYCOL, ETHYLHEXYLGLYCERIN, ACRYLATES/C10-30 ALKYL ACRYLATE CROSSPOLYMER, TRIETHANOLAMINE

PURPOSE

ANTISEPTIC, ANTIMICROBIAL, ANTI-BACTERIAL, ANTI-VIRUS

WARNINGS

For external use only.
Flammable. Keep away from heat or flame
--------------------------------------------------------------------------------------------------------
Do not use
• In children less than 2 months of age
• Avoid contact with broken skin
--------------------------------------------------------------------------------------------------------
When using this product keep out of eyes, ears, and mouth. In case of contact with eyes, rinse eyes thoroughly with water.
--------------------------------------------------------------------------------------------------------
Stop use and ask a doctor if skin irritation occurs and consult a doctor immediately.

KEEP OUT OF REACH OF CHILDREN

If swallowed, get medical help or contact a Poison Control Center right away.

Uses

This rinse-free hand gel moisturizers the hands while cleaning, it also refreshes and reduces bacterial growth through silver ions released from MICROSILVER

Directions

• Apply liberally as often as needed.
• Slight trace of pure silver powder is normal and not harmful.
• Please SHAKE WELL before use.

Other information

• Store in a cool, dry place, keep away from direct sunlight.
• Store between 15-30C (59-86F)
• Avoid freezing and excessive heat above 40C (104F)